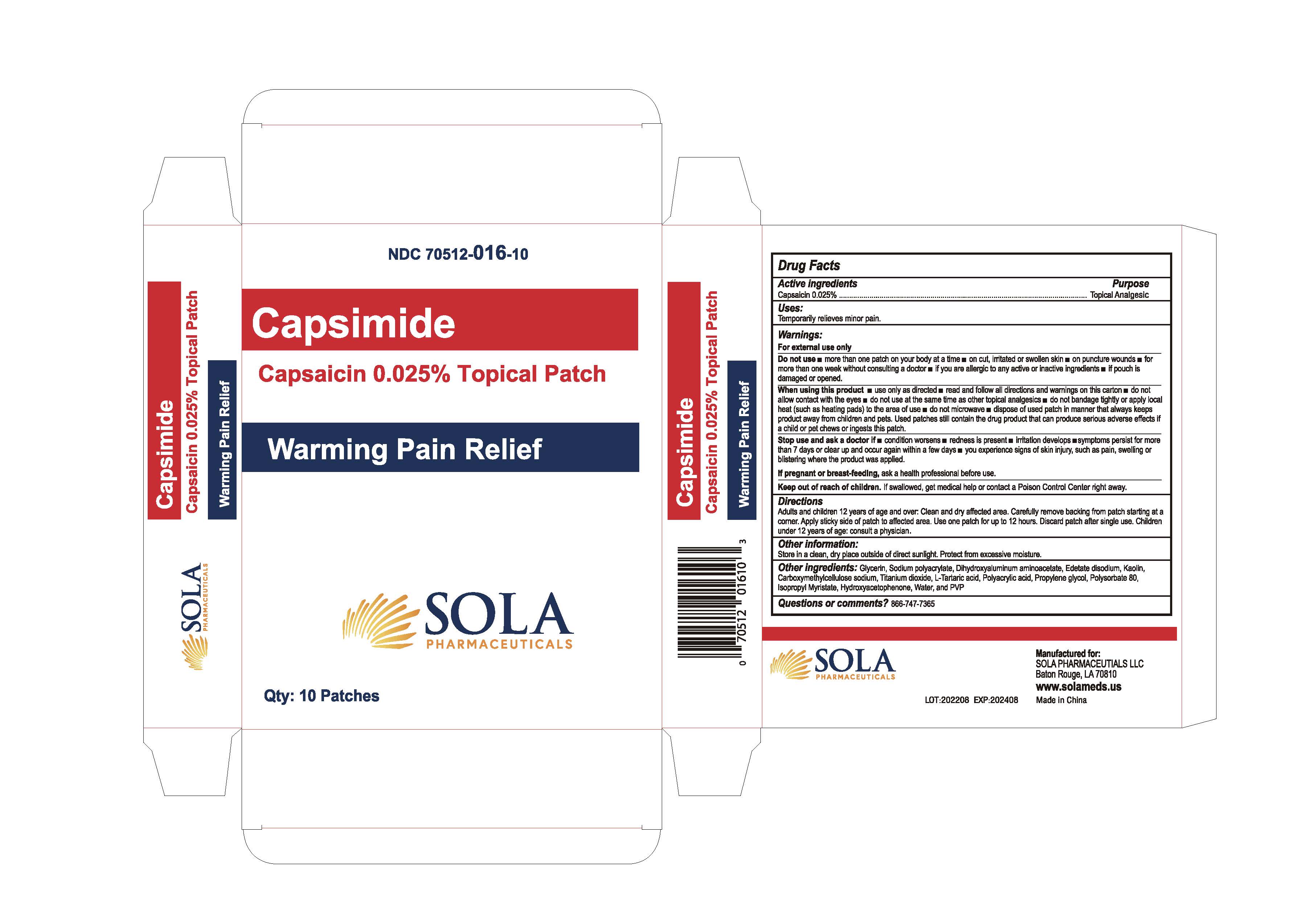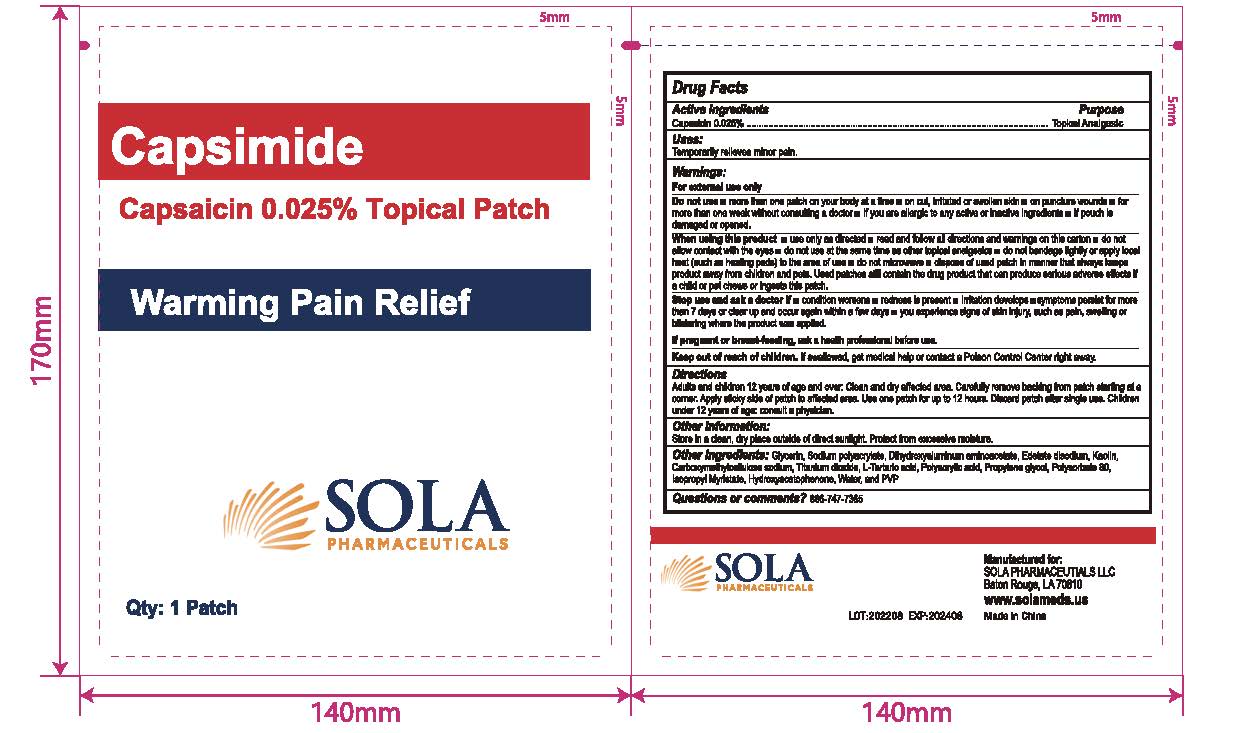 DRUG LABEL: Capsimide
NDC: 70512-016 | Form: PATCH
Manufacturer: Sola Pharmaceuticals
Category: otc | Type: HUMAN OTC DRUG LABEL
Date: 20251208

ACTIVE INGREDIENTS: CAPSAICIN 0.025 g/100 g
INACTIVE INGREDIENTS: PROPYLENE GLYCOL; HYDROXYACETOPHENONE; WATER; DIHYDROXYALUMINUM AMINOACETATE; EDETATE DISODIUM; KAOLIN; CARBOXYMETHYLCELLULOSE SODIUM; SODIUM POLYACRYLATE (8000 MW); POVIDONE; TITANIUM DIOXIDE; TARTARIC ACID; POLYACRYLIC ACID (8000 MW); POLYSORBATE 80; ISOPROPYL MYRISTATE; GLYCERIN

Capsimide Patch

Active Ingredients

Capsaicin 0.025%

Purpose

Topical Analgesic

Uses

Temporarily relieves minor pain.

Warnings

For external use only

Do not use

- more than one patch on your body at a time
- on cut, irritated or swollen skin
- on puncture wounds
- for more than one week without consulting a doctor
- if you are allergic to any active or inactive ingredients
- if pouch is damaged or opened

When using this product

- use only as directed
- read and follow all directions and warnings on this carton
- do not allow contact with the eyes
- do not sue at the same time as other topical analgesics
- do not bandage tightly or apply local heat (such as heating pads) to the area of use
- do not microwave
- dispose of used patch in a manner that always keeps product away from children and pets. Used patches still contain the drug product that can produce serious adverse effects if a child or pet chews or ingests this patch.

Stop use and ask a doctor if

- condition worsens
- redness is present
- irritation develops
- symptoms persist for more than 7 days or clear up and occur again within a few days
- you experience signs of skin injury, such as pain, swelling or blistering where the product was applied.

If pregnant or breast-feeding

ask a health professional before use.

Keep our of reach of children

If swallowed, get medical help or contact a Poison Control Center right away.

Directions

Adults and children 12 years of age and over: Clean and dry affected area. Carefully remove backing from patch starting at a corner. Apply sticky side of patch to affected area. Use one patch for up to 12 hours. Discard patch after single use. Children under 12 years of age: consuly a physician.

Other Information

Store in a clean, dry place outside of direct sunlight. Protect from excessive moisture.

Other Ingredients

Glycerin, Sodium polyacrylate, Dihydroxyaluminum aminoacetate, Edetate disodium, Kaolin, Carboxymethylcellulose sodium, Titanium dioxide, L-Tartaric acid, Polyacrylic acid, Propylene glycol, Polysorbate 80, Isopropyl Myristate, Hydroxyacetophenone, Water, and PVP

Questions or comments?

866-747-7365

PACKAGE LABEL

Manufactured for:

SOLA PHARMACEUTICALS LLC

Baton Rouge, LA 70810

www.solameds.us

Made in China

Capsimide Patch

NDC 70512-016-10

Qty: 10 Patches

(1 per pouch) x 10